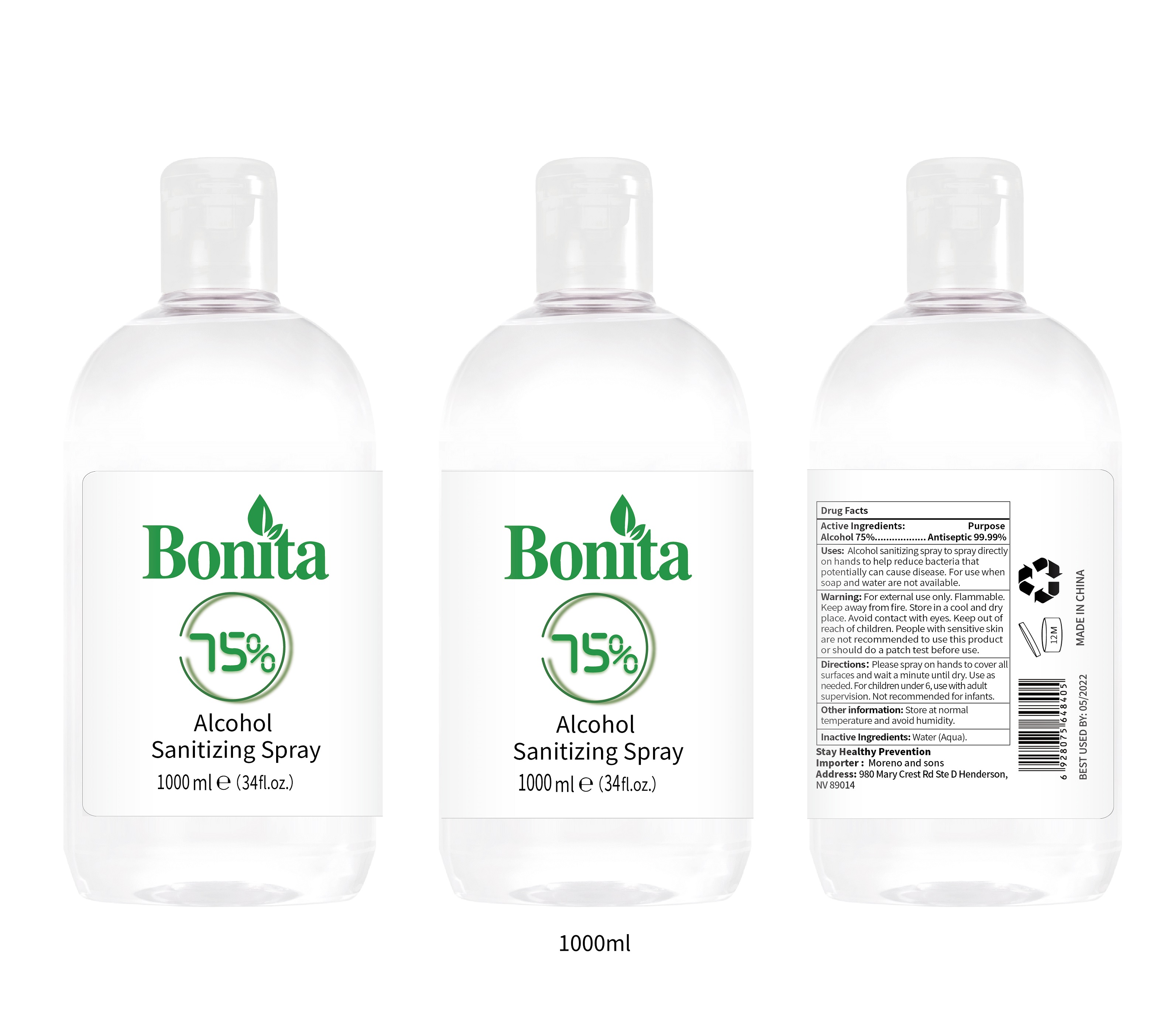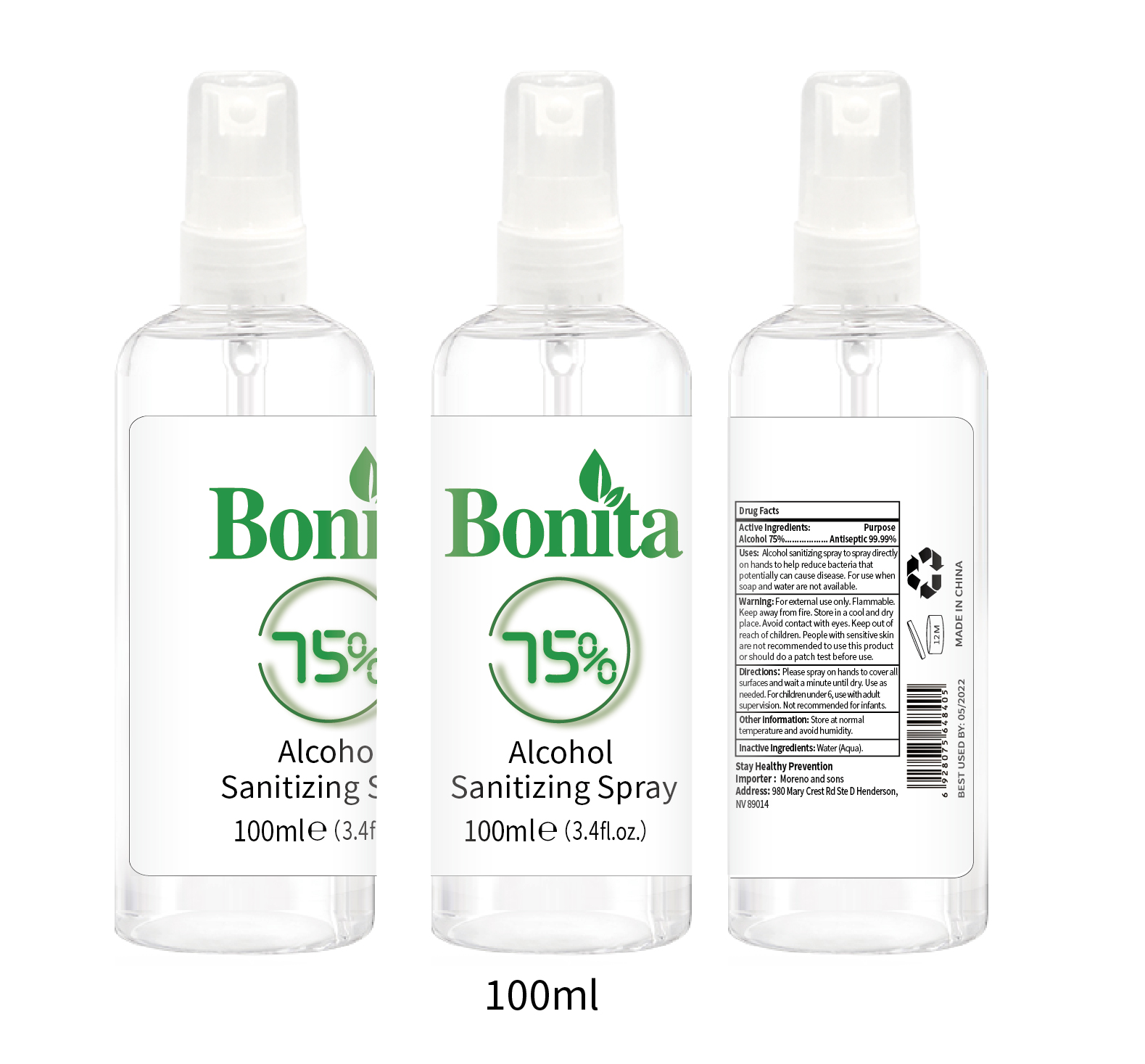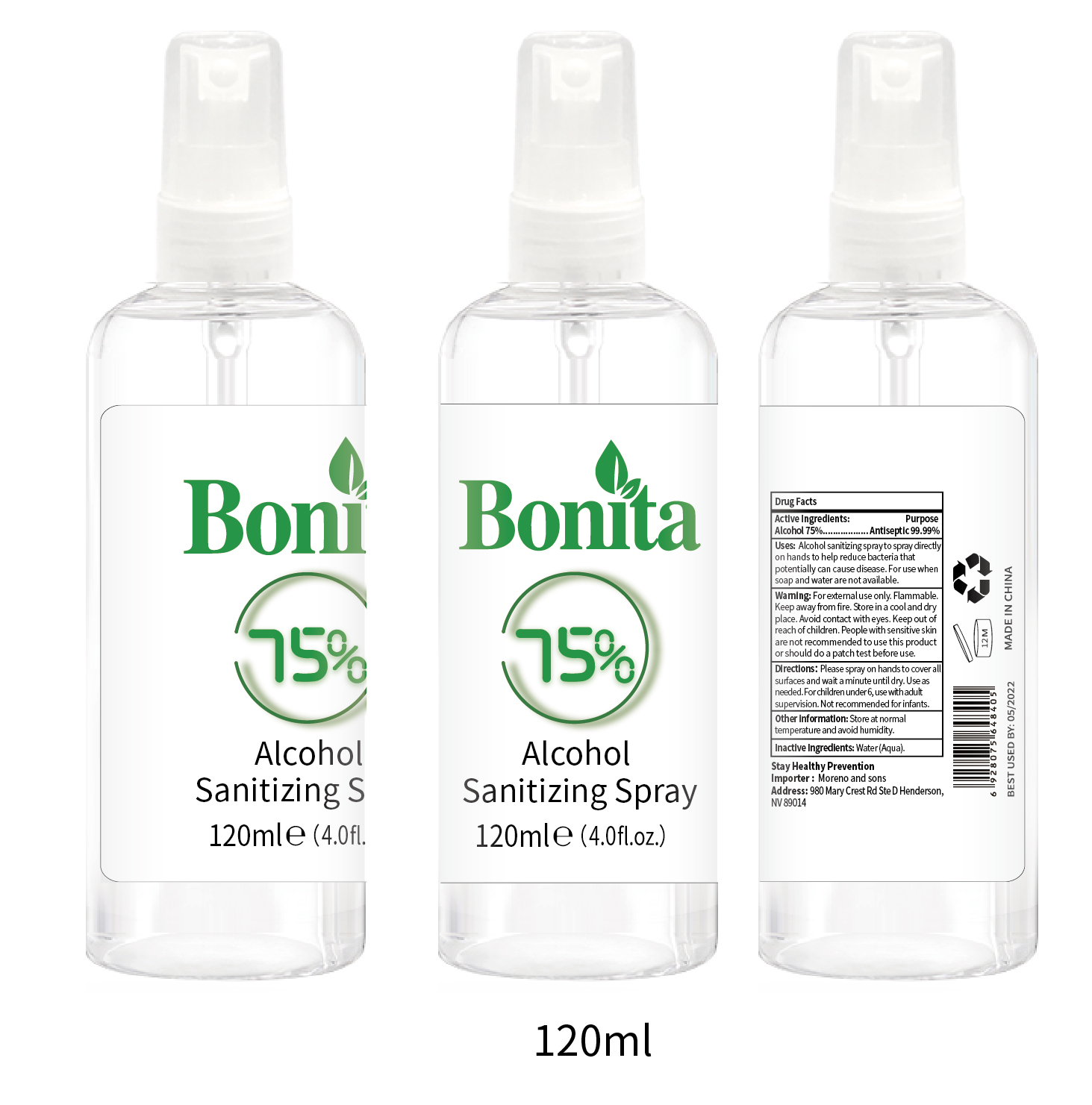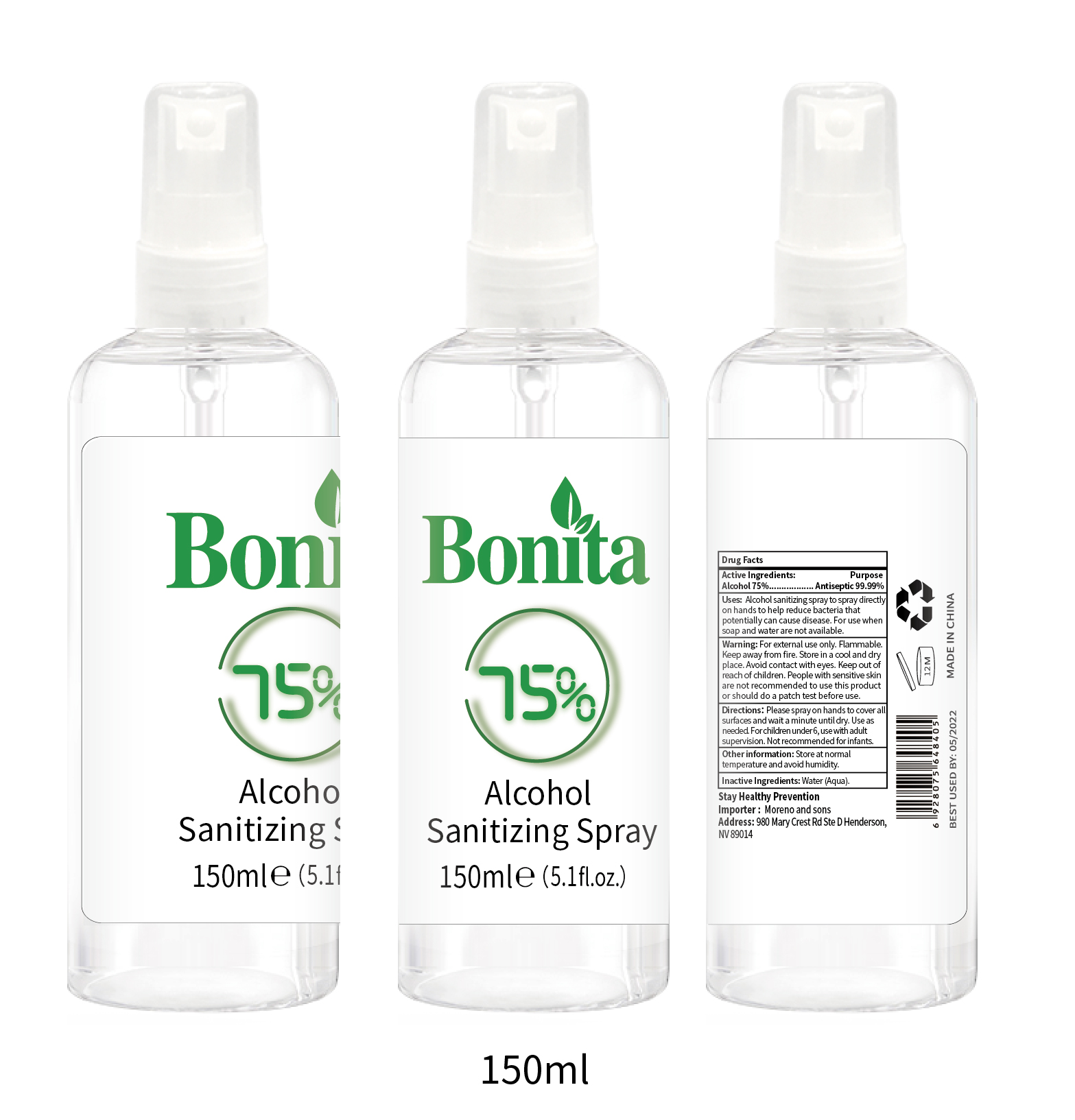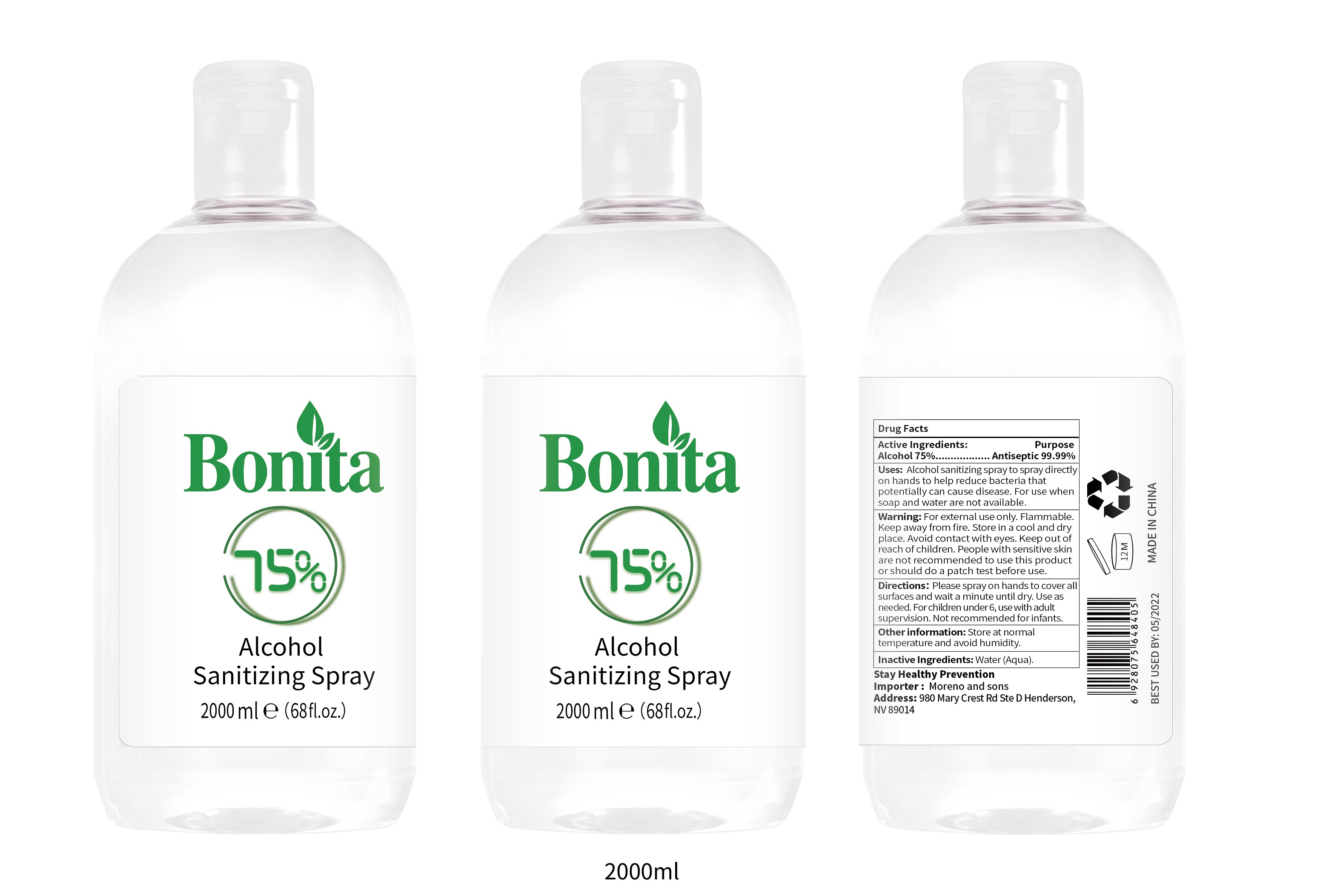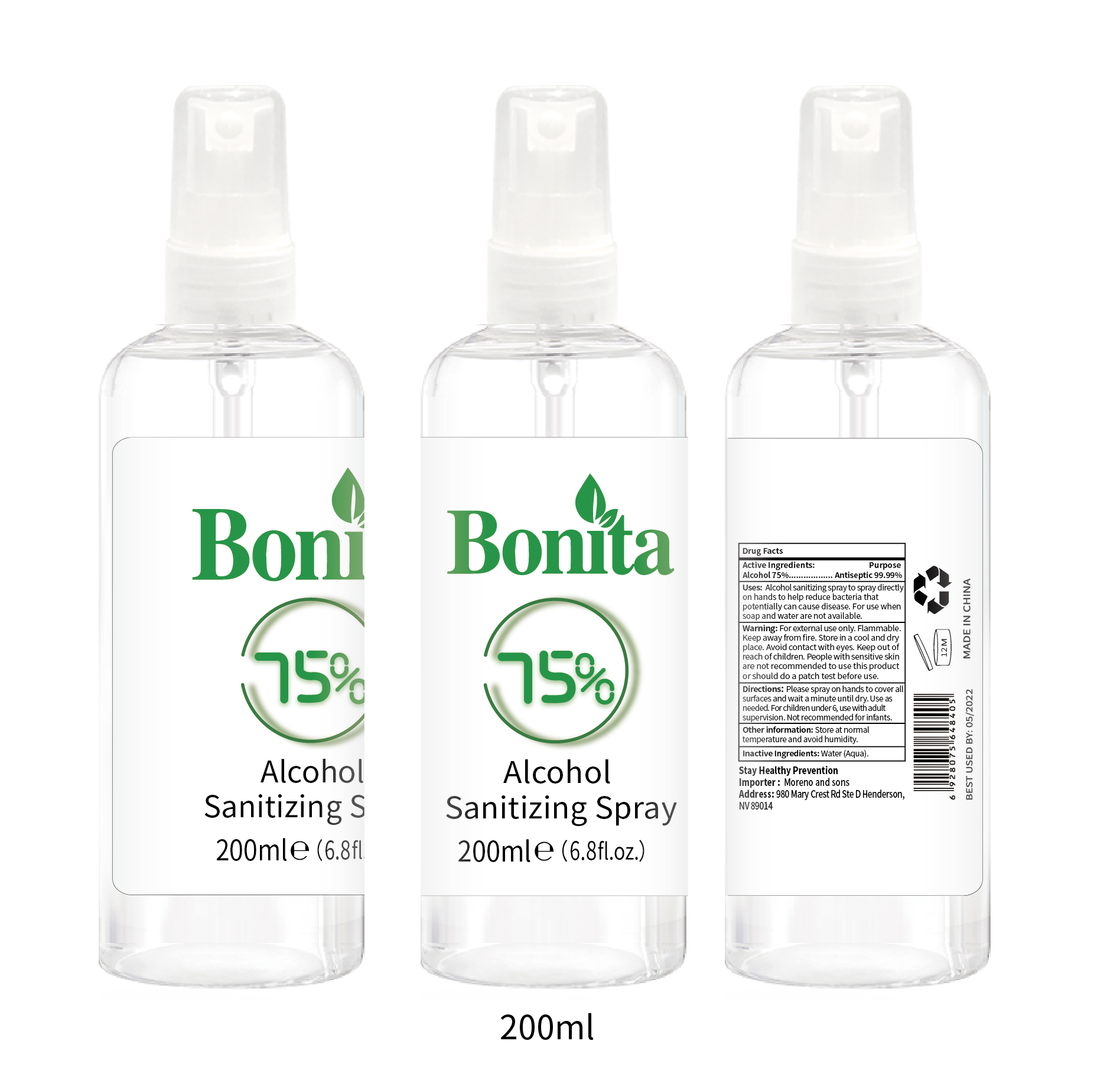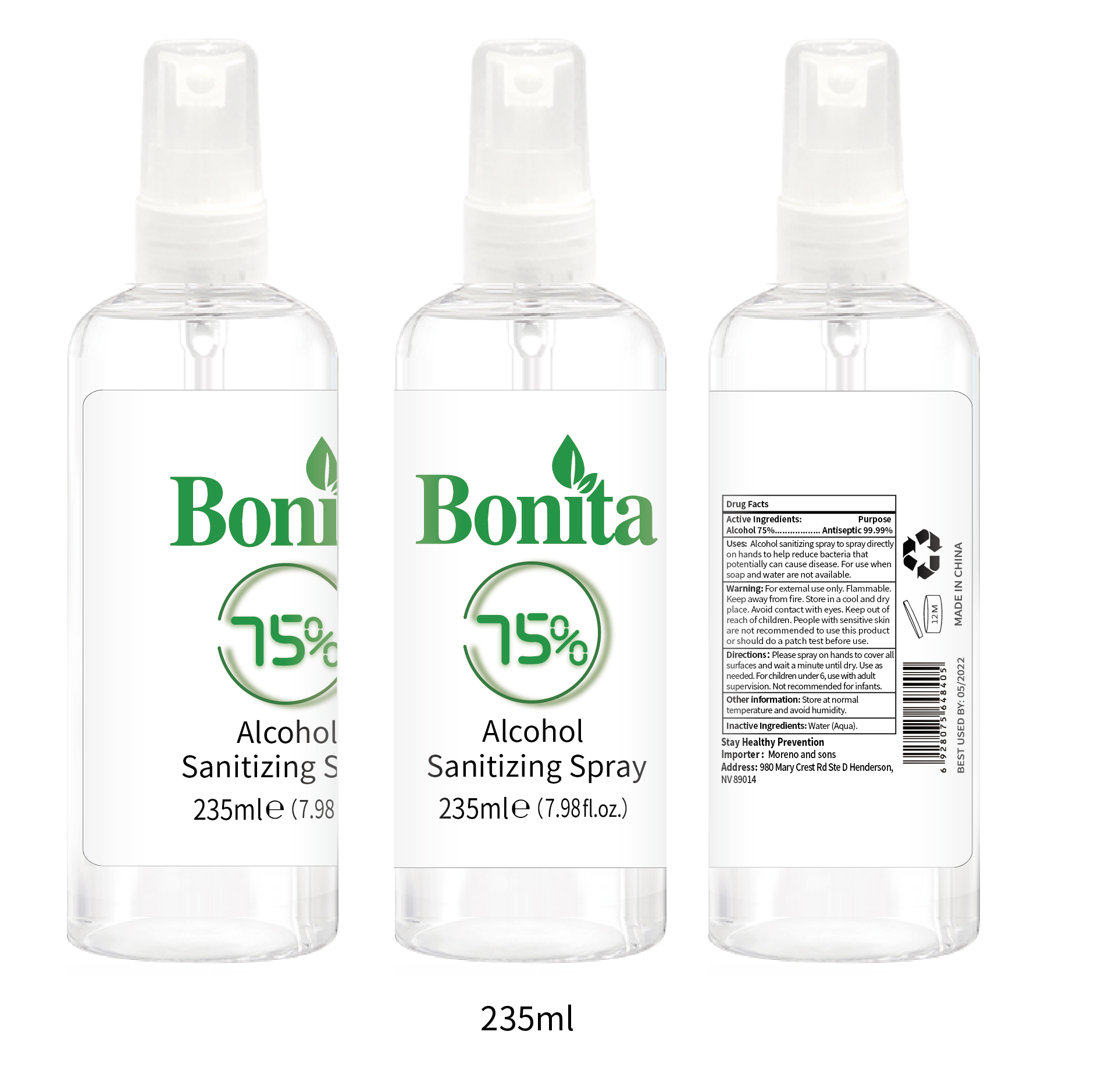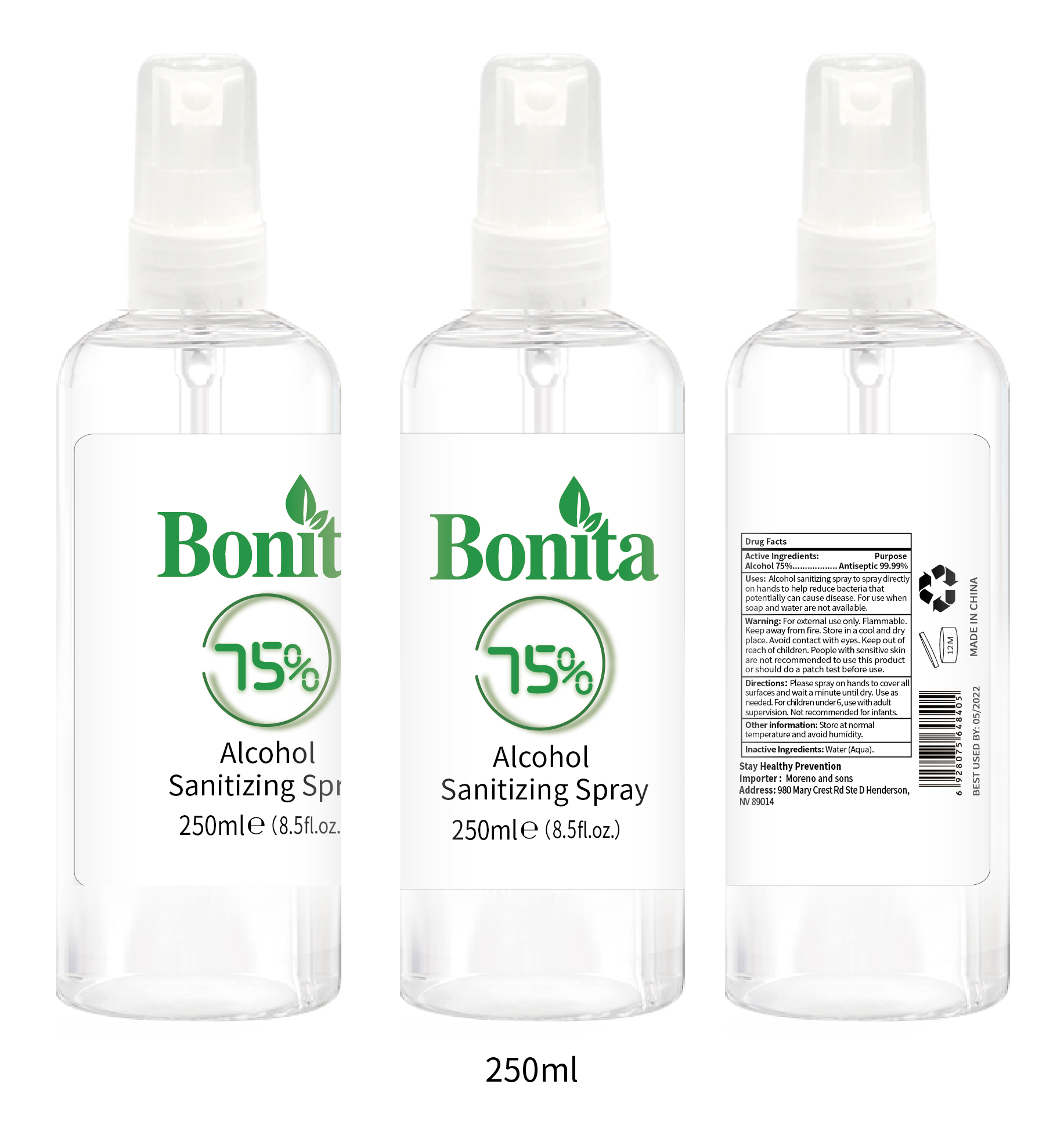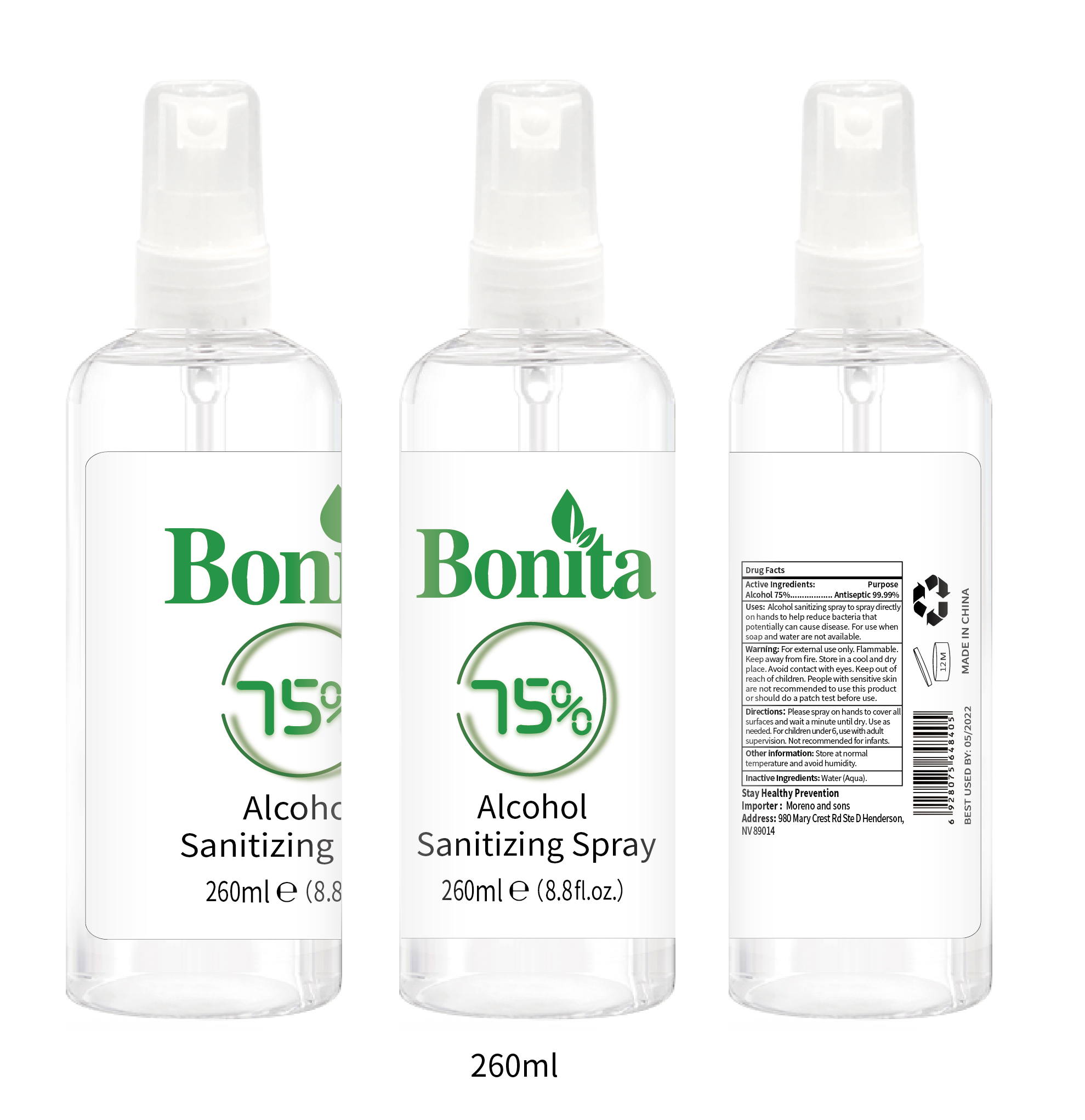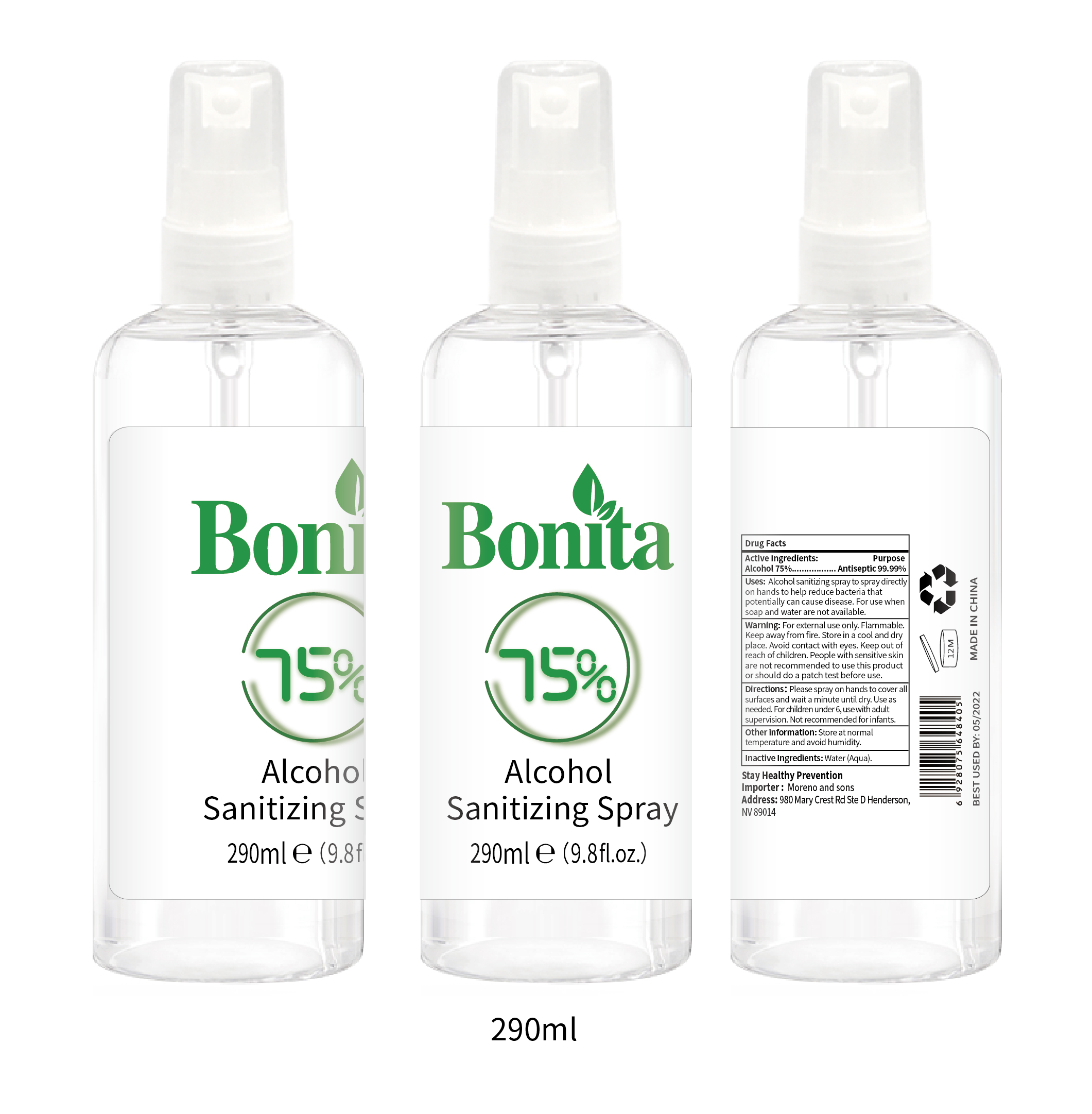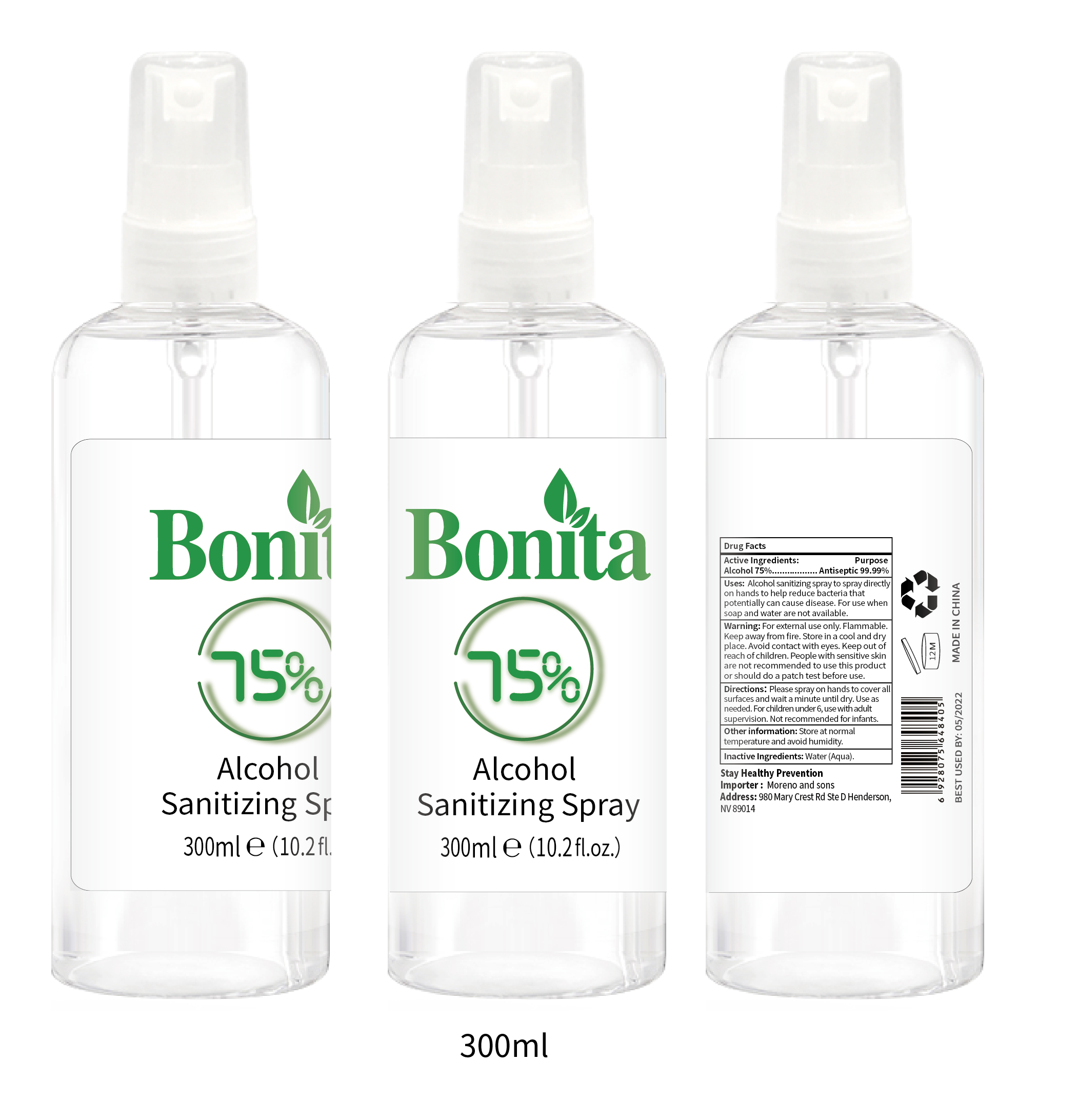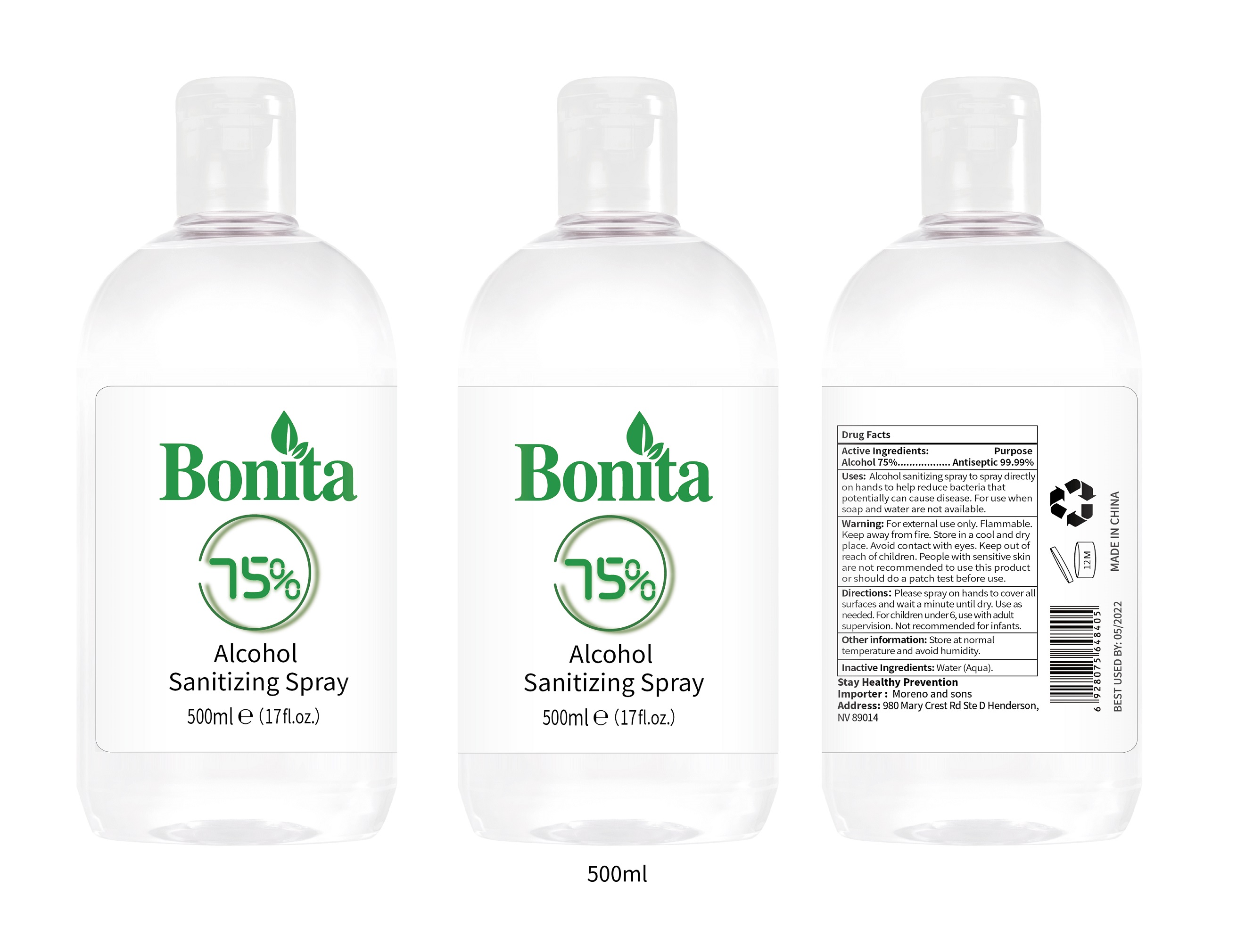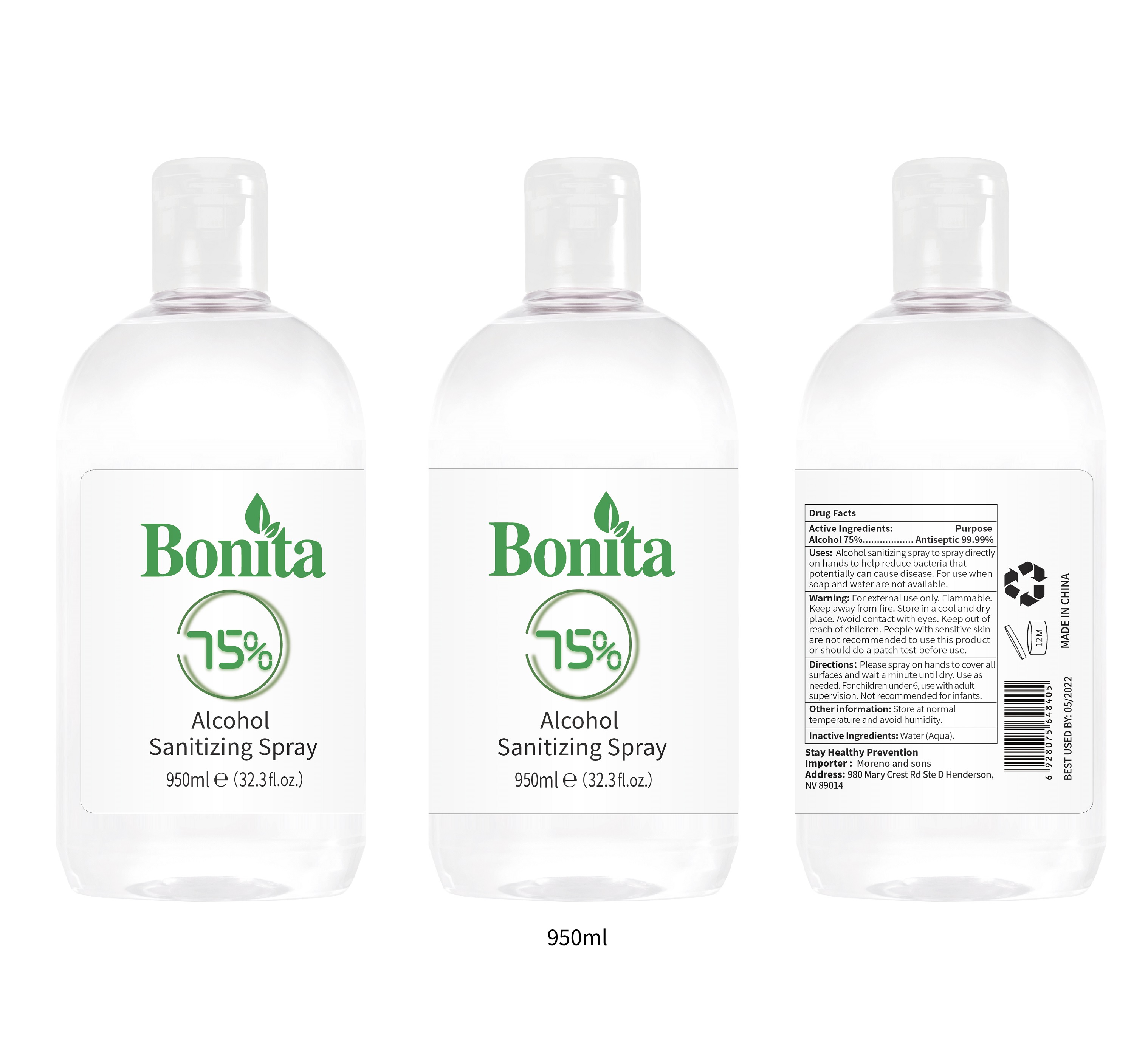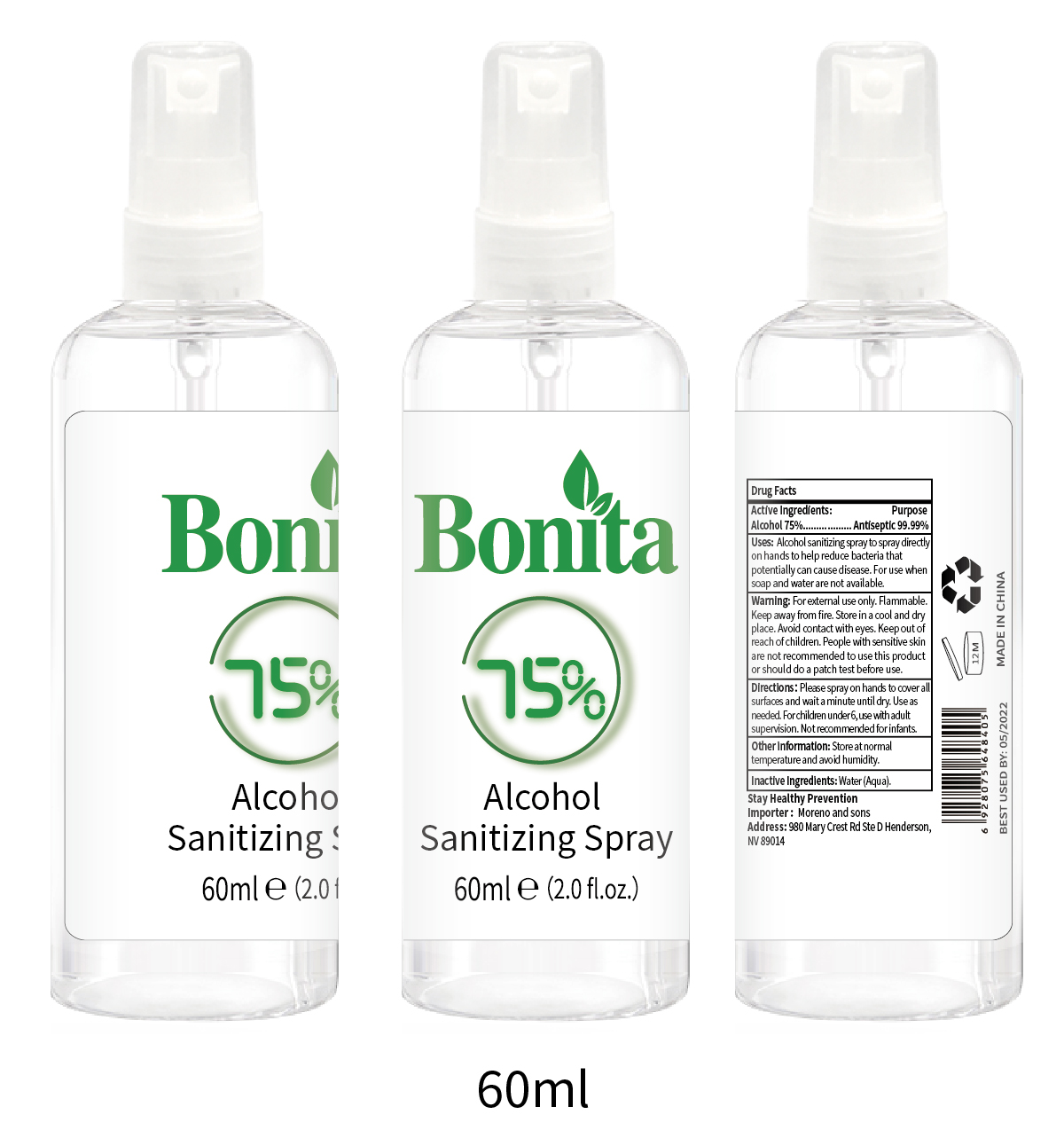 DRUG LABEL: Bonita Alcohol Sanitizing
NDC: 78409-001 | Form: SPRAY
Manufacturer: Moreno and Sons Company
Category: otc | Type: HUMAN OTC DRUG LABEL
Date: 20211104

ACTIVE INGREDIENTS: ALCOHOL 75 mL/100 mL
INACTIVE INGREDIENTS: WATER 25 mL/100 mL

Bonita Alcohol Sanitizing Spray

Active Ingredients:

Alcohol 75%

Purpose

Antiseptic 99.99%

Uses:

Alcohol sanitizing spray to spray directly on hands to help reduce bacteria that potentially can cause disease. For use when soap and water are not available.

Warning:

For external use only. Flammable. Keep away from fire. Store in a cool and dry place. Avoid contact with eyes. Keep out of reach of children. People with sensitive skin are not recommended to use this product or should do a patch test before use.

Keep out of reach of children.

Directions：

Please spray on hands to cover all surfaces and wait a minute until dry. Use as needed. For children under 6, use with adult supervision. Not recommended for infants.

Other information:

Store at normal temperature and avoid humidity.

Inactive Ingredients:

Water (Aqua).

Package Label

Bonita

75%

Alcohol Sanitizing Spray

60ml e (2.0 fl.oz.)

NDC: 78409-001-01

Package Label

Bonita

75%

Alcohol Sanitizing Spray

100ml e (3.4 fl.oz.)

Package Label

Bonita

75%

Alcohol Sanitizing Spray

120ml e (4.0 fl.oz.)

Package Label

Bonita

75%

Alcohol Sanitizing Spray

150ml e (5.1 fl.oz.)

Package Label

Bonita

75%

Alcohol Sanitizing Spray

200ml e (6.8 fl.oz.)

Package Label

Bonita

75%

Alcohol Sanitizing Spray

235ml e (7.98 fl.oz.)

Package Label

Bonita

75%

Alcohol Sanitizing Spray

250ml e (8.5 fl.oz.)

Package Label

Bonita

75%

Alcohol Sanitizing Spray

260ml e (8.8 fl.oz.)

Package Label

Bonita

75%

Alcohol Sanitizing Spray

290ml e (9.8 fl.oz.)

Package Label

Bonita

75%

Alcohol Sanitizing Spray

300ml e (10.2 fl.oz.)

Package Label

Bonita

75%

Alcohol Sanitizing Spray

500ml e (17 fl.oz.)

Package Label

Bonita

75%

Alcohol Sanitizing Spray

950ml e (32.3 fl.oz.)

Package Label

Bonita

75%

Alcohol Sanitizing Spray

1000ml e (34 fl.oz.)

Package Label

Bonita

75%

Alcohol Sanitizing Spray

2000ml e (68 fl.oz.)